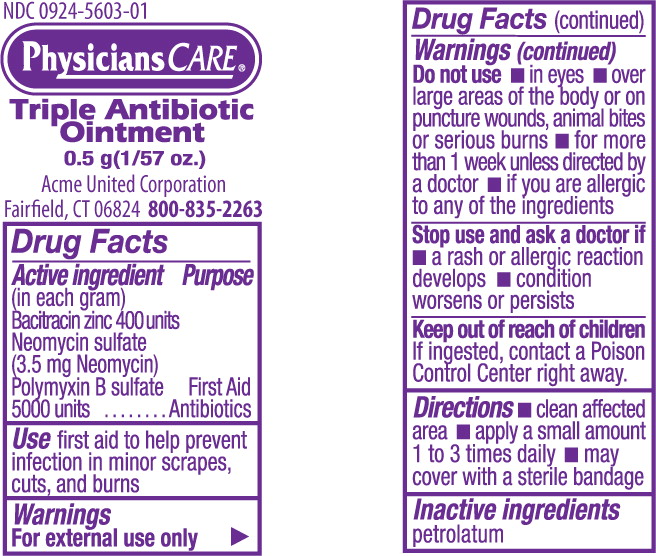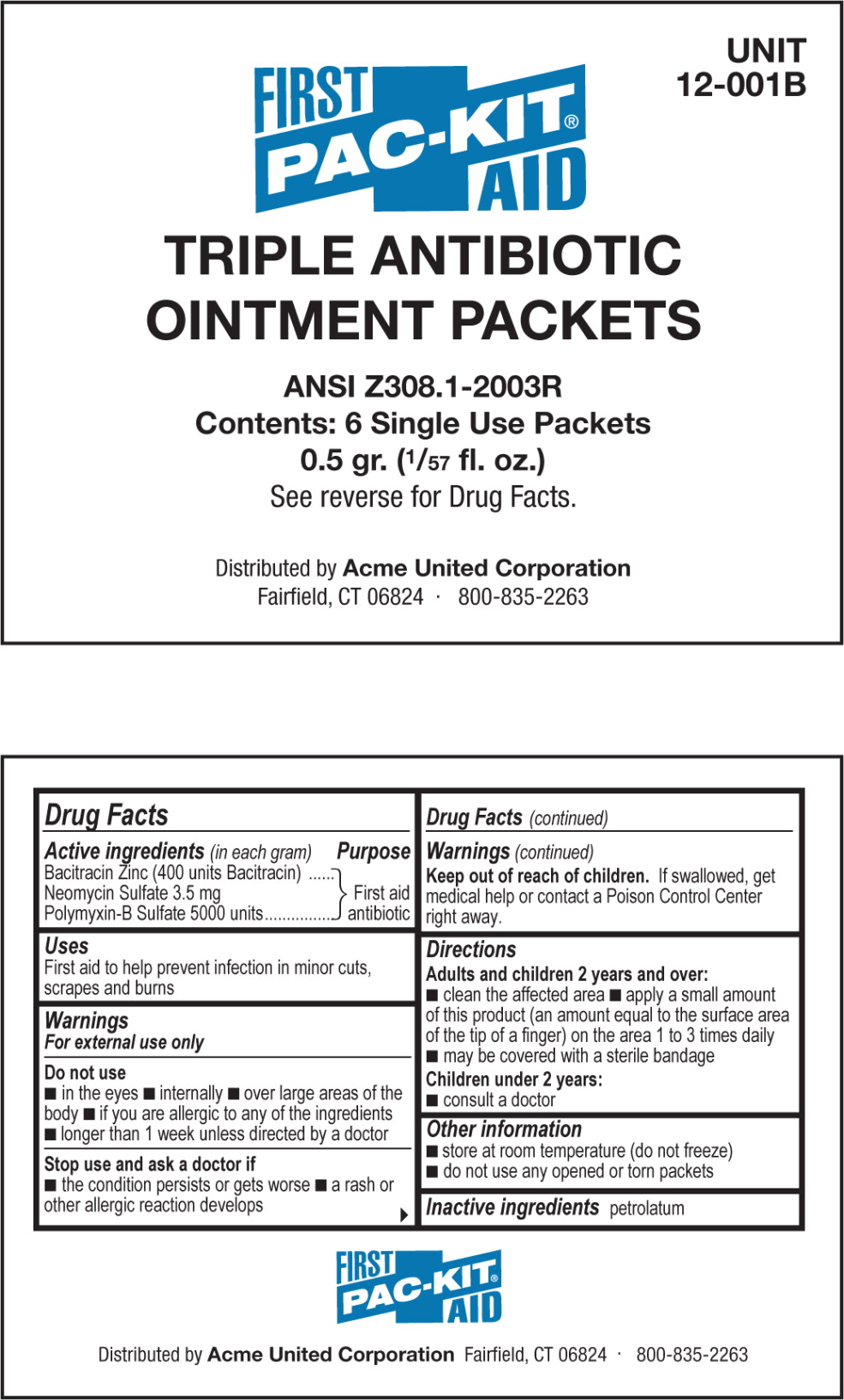 DRUG LABEL: triple antibiotic
NDC: 0924-5603 | Form: OINTMENT
Manufacturer: Acme United Corporation
Category: otc | Type: HUMAN OTC DRUG LABEL
Date: 20120127

ACTIVE INGREDIENTS: bacitracin zinc 400 [iU]/1 g; neomycin sulfate 3.5 mg/1 g; polymyxin b sulfate 5000 [iU]/1 g
INACTIVE INGREDIENTS: petrolatum

Drug Facts

Active Ingredients (in each gram)

Bacitracin Zinc (400 units Bacitracin)

Neomycin Sulfate 3.5 mg

Polymyxin-B Sulfate 5000 units

Purpose

First Aid Antibiotics

Uses

first aid to help prevent infection in minor cuts, scrapes, and burns

Warnings

For external use only

Do not use

- in eyes
- internally
- over large areas of the body
- if you are allergic to any of the ingredients
- for more than 1 week unless directed by a doctor

Stop use and ask a doctor if

- the condition persists or gets worse
- a rash or other allergic reaction develops

Keep out of reach of children.

If swallowed, get medical help or contact a Poison Control Center right away

Directions

Adults and children 2 years and over:

- clean the affected area
- apply a small amount of this product (an amount equal to the surface area of the tip of a finger) on the area 1 to 3 times daily
- may cover with a sterile bandage

Children under 2 years:

- consult a doctor

Other information

- store at room temperature (do not freeze)
- do not use any opened or torn packets

Inactive ingredients

petrolatum

PRINCIPAL DISPLAY PANEL – packet

NDC 0924-5603-01

PhysiciansCARE

Triple Antibiotic
Ointment

0.5 g (1/57 oz.)

Acme United Corporation

Fairfield, CT 06824 800-835-2263

PRINCIPAL DISPLAY PANEL – bag

UNIT
12-001B

PAC-KIT FIRST AID

Triple Antibiotic
Ointment Packets

ANSI Z308.1-2003R
Contents: 6 Single Use Packets
0.5 gr. (1/57 fl. oz.)
See reverse for Drug Facts

Distributed by Acme United Corporation
Fairfield, CT 06824 · 800-835-2263